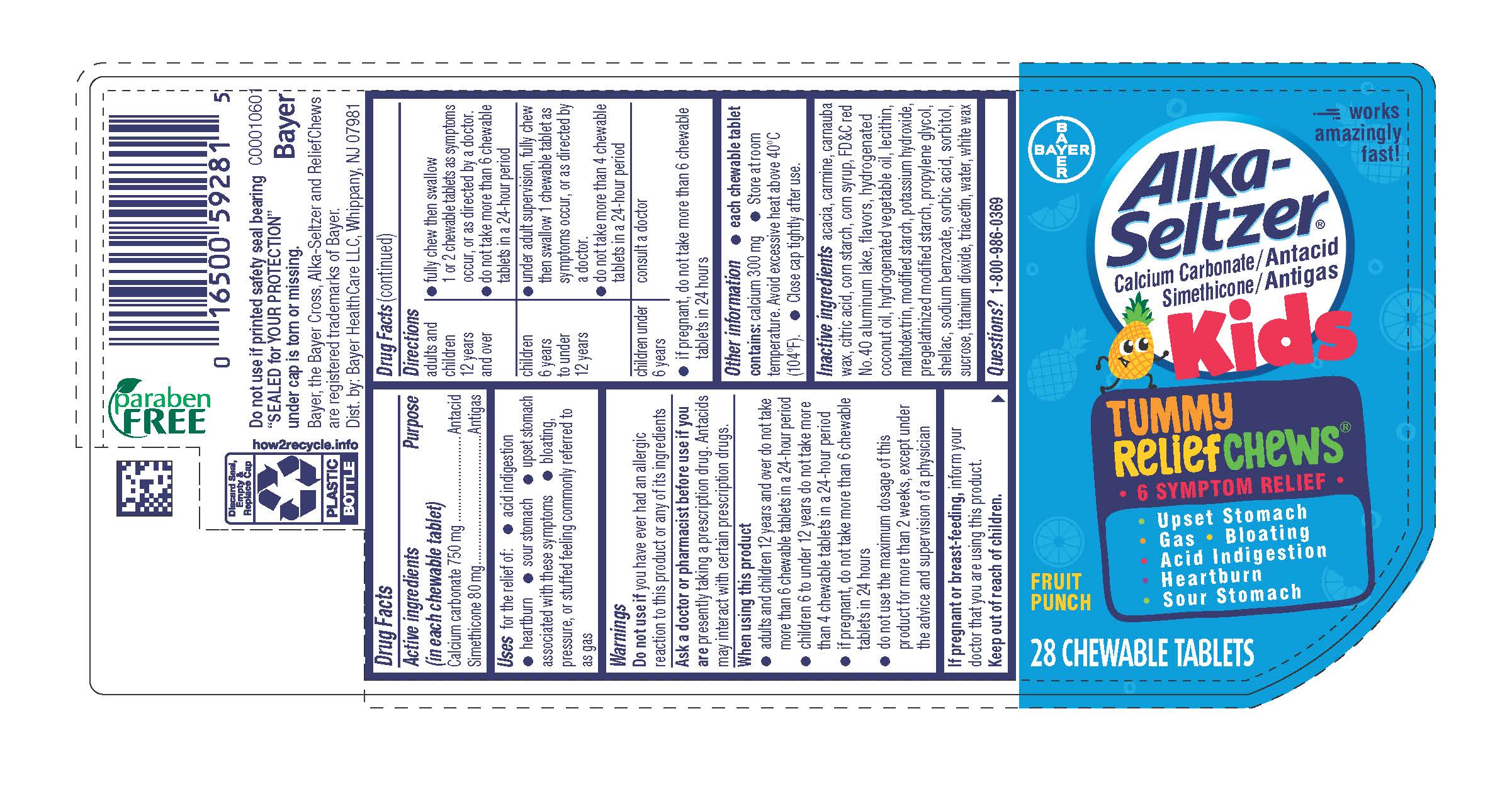 DRUG LABEL: Alka-Seltzer Kids Tummy ReliefChews
NDC: 0280-0051 | Form: TABLET, CHEWABLE
Manufacturer: Bayer HealthCare LLC.
Category: otc | Type: HUMAN OTC DRUG LABEL
Date: 20251204

ACTIVE INGREDIENTS: CALCIUM CARBONATE 750 mg/1 1; DIMETHICONE 80 mg/1 1
INACTIVE INGREDIENTS: TITANIUM DIOXIDE; TRIACETIN; SORBITOL; MODIFIED CORN STARCH (1-OCTENYL SUCCINIC ANHYDRIDE); WATER; WHITE WAX; SHELLAC; ACACIA; CORN SYRUP; MALTODEXTRIN; METHYLPARABEN; CARNAUBA WAX; POTASSIUM HYDROXIDE; FD&C RED NO. 40; HYDROGENATED COCONUT OIL; PROPYLPARABEN; SORBIC ACID

Alka-Seltzer Kids Tummy ReliefChews UI 1611515

Drug Facts

Active ingredients and purpoose

Active ingredients (in each chewable tablet) Purpose
Calcium carbonate 750 mg….................................….…...Antacid
Simethicone 80 mg……………………………………….......Antigas

INDICATIONS AND USAGE

Uses for the relief of:
● acid indigestion ● heartburn ● sour stomach
● upset stomach associated with these symptoms
● bloating, pressure, or stuffed feeling commonly referred to as gas

Warnings

Do not use if you have ever had an allergic reaction to this product or any of its ingredients

Ask a doctor or pharmacist before use if you are presently taking a prescription drug. Antacids may interact with certain prescription drugs.

When using this product
● adults and children 12 years and over do not take more than 6 chewable tablets in a 24-hour period
● children 6 to under 12 years do not take more than 4 chewable tablets in a 24-hour period
● if pregnant, do not take more than 6 chewable tablets in 24 hours
● do not use the maximum dosage of this product for more than 2 weeks, except under the advice and supervision of a
physician

PREGNANCY OR BREAST FEEDING

If pregnant or breast-feeding, inform your doctor that you are using this product.

Keep out of reach of children.

Directions

adults and children 12 years and over | • fully chew then swallow 1 or 2 chewable tablets as symptoms occur, or as directed by a doctor. • do not take more than 6 chewable tablets in a 24-hour period
children 6 years to under 12 years | • under adult supervision, fully chew then swallow 1 chewable tablet as symptoms occur, or as directed by a doctor. • do not take more than 4 chewable tablets in a 24-hour period
children under 6 years | consult a doctor

- if pregnant, do not take more than 6 chewable tablets in 24 hours

Other information
● each chewable tablet contains: calcium 300 mg
● store at room temperature. Avoid excessive heat above 40°C (104°F).
● close cap tightly after use

INACTIVE INGREDIENT

Inactive ingredients acacia, carmine, carnauba wax, citric acid, corn starch, corn syrup, FD&C red No.40 aluminum lake, flavors, hydrogenated coconut oil, hydrogenated vegetable oil, lecithin, maltodextrin, modified starch, potassium hydroxide, pregelatinized modified starch, propylene glycol, shellac, sodium benzoate, sorbic acid, sorbitol, sucrose, titanium dioxide, triacetin, water, white wax

Questions or comments? 1-800-986-0369 (Mon – Fri 9AM – 5PM EST)

Package label 28 count

Works

Amazingly

Fast!

Alka-Seltzer® Kids

Tummy ReliefChews®

Calcium Carbonate/Antiacid

Simethicone/Antigas

•6 Symptom Relief•

•Upset Stomach

•Gas • Bloating

•Acid Indigestion

•Heartburn

•Upset Stomach

FRUIT PUNCH

28 CHEWABLE TABLETS